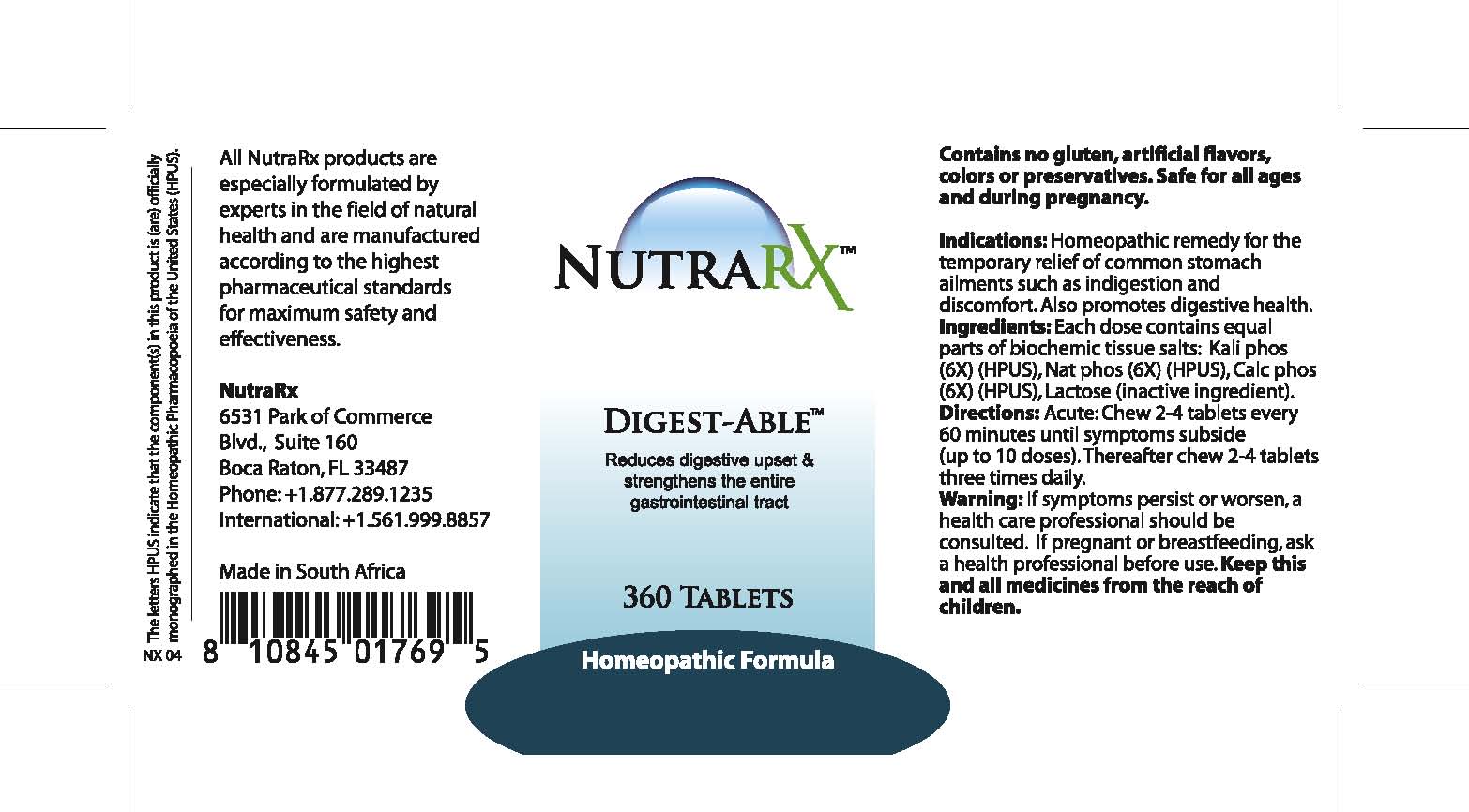 DRUG LABEL: NutraRX Digest-Able
NDC: 68647-194 | Form: TABLET
Manufacturer: Feelgood Health
Category: homeopathic | Type: HUMAN OTC DRUG LABEL
Date: 20100923

ACTIVE INGREDIENTS: POTASSIUM PHOSPHATE, DIBASIC 6 [hp_X]/1 1; SODIUM PHOSPHATE, DIBASIC ANHYDROUS 6 [hp_X]/1 1; TRIBASIC CALCIUM PHOSPHATE 6 [hp_X]/1 1
INACTIVE INGREDIENTS: LACTOSE

NUTRARX DIGEST-ABLE

PURPOSE

Reduces digestive upset and strengthens the entire gastrointestinal tract

INDICATIONS AND USAGE

Indications: Homeopathic remedy for the temporary relief of common stomach ailments such as indigestion and discomfort. Also promotes digestive health.

DOSAGE AND ADMINISTRATION

Directions: Acute: Chew 2-4 tablets every 60 minutes until symptoms subside (up to 10 doses). Thereafter chew 2-4 tablets three times daily.

GENERAL PRECAUTIONS

Warning: If symptoms persist or worsen, a health care professional should be consulted.Keep this and all medicines from the reach of children.

ACTIVE INGREDIENT

Ingredients: Each dose contains equal parts of biochemic tissue salts:Kali phos (6X) (HPUS), Nat phos (6X) (HPUS), Calc phos (6X) (HPUS)

Lactose (inactive ingredient).

PREGNANCY

If pregnant or breastfeeding, ask a health professional before use.

WARNINGS

Contains no gluten, artificial flavors, colors or preservatives. Safe for all ages and during pregnancy.

PATIENT COUNSELING INFORMATION

All NutraRx products are especially formulated by experts in the field of natural health and are manufactured according to the highest pharmaceutical standards for maximum safety and effectiveness.

NutraRx

6531 Park of Commerce

Blvd., Suite 160

Boca Raton, FL 33487

Phone: +1.877.289.1235

International: +1.561.999.8857

Made in South Africa

The letters HPUS indicate that the component(s) in this product is (are) officially monographed in the Homeopathic Pharmacopoeia of the United States (HPUS).

KEEP OUT OF REACH OF CHILDREN

Keep this and all medicines from the reach of children.